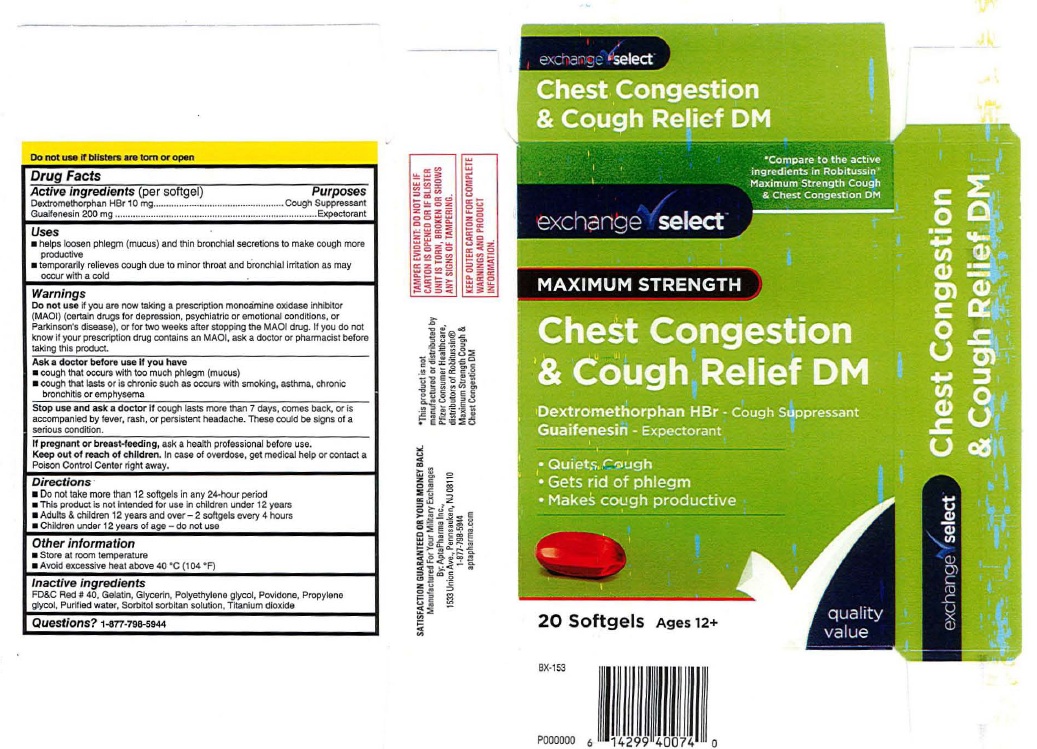 DRUG LABEL: Chest Congestion and Cough Relief DM
NDC: 55301-601 | Form: CAPSULE, LIQUID FILLED
Manufacturer: ARMY AND AIR FORCE EXCHANGE SERVICE
Category: otc | Type: HUMAN OTC DRUG LABEL
Date: 20251219

ACTIVE INGREDIENTS: DEXTROMETHORPHAN HYDROBROMIDE 10 mg/1 1; GUAIFENESIN 200 mg/1 1
INACTIVE INGREDIENTS: FD&C RED NO. 40; GELATIN; GLYCERIN; POLYETHYLENE GLYCOL, UNSPECIFIED; POVIDONE; PROPYLENE GLYCOL; WATER; SORBITOL; SORBITAN; TITANIUM DIOXIDE

exchange select Chest Congestion & Cough Relief DM

Drug Facts
Active ingredients (per softgel)
Dextromethorphan HBr 10 mg
Guaifenesin 200 mg

Purposes
Dextromethorphan HBr ..........................Cough Suppressant
Guaifenesin ....................................Expectorant

Uses
■ helps loosen phlegm (mucus) and thin broochial secretions to make cough more
productlve
■ temporarily relieves cough due to minor throat and bronchial irritation as may
occur with a cold

Warnings
Do not use if you are now taking a prescription monoamine oxidase inhibitor
(MAOI) (certain drugs for depression, psychiatric or emotional conditions, or
Parkinson's disease), or for two weeks after stopping the MAOI drug. If you do not
know if your prescription drug contains an MAOI, ask a doctor or pharmacist before
taking this product.

Ask a doctor before use if you have
■ cough that occurs with too much phlegm (mucus)
■ cough that lasts or is chronic such as occurs with smoking, asthma, chronic
bronchitis or emphysema

Stop use and ask a doctor ifcough lasts more than 7 days, comes back, or is
accompanied by fever, rash, or persistent headache. These could be signs of a
serious condition.

PREGNANCY OR BREAST FEEDING

If pregnant or breast-feeding, ask a health professional before use.

Keep out of reach of children.

In case of overdose, get medical help or contact a
Poison Control Center right away.

Directions
■ Do not take more than 12 softgels in any 24·hour period
■ This product is nol lntended for use in children under 12 years
■ Adults & children 12 years and over - 2 softgels every 4 hours
■ Children under 12 years of age - do not use

Other information
■ Store at room temperature
■ Avoid excessive heat above 40'C (104'F)

Inactive ingredients
FD&C Red # 40, Gelatin, Glycerin, Polyethylene glycol, Povidone, Propylene
glycol, Purified water, Sorbitol sorbllan solulion, Titanium dioxide

Questions? 1-877-798-5944

Product Label: exchange select Chest Congestion & Cough Relief DM

exchange select

Chest Congestion

& Cough Relief DM

20 Softgels Ages 12+

Manufactured For Your Military Exchange

By AptaPharma Inc.,

1533 Union Avenue, Pennsauken, NJ 08110

1-877-798-5944

aptapharma.com

res